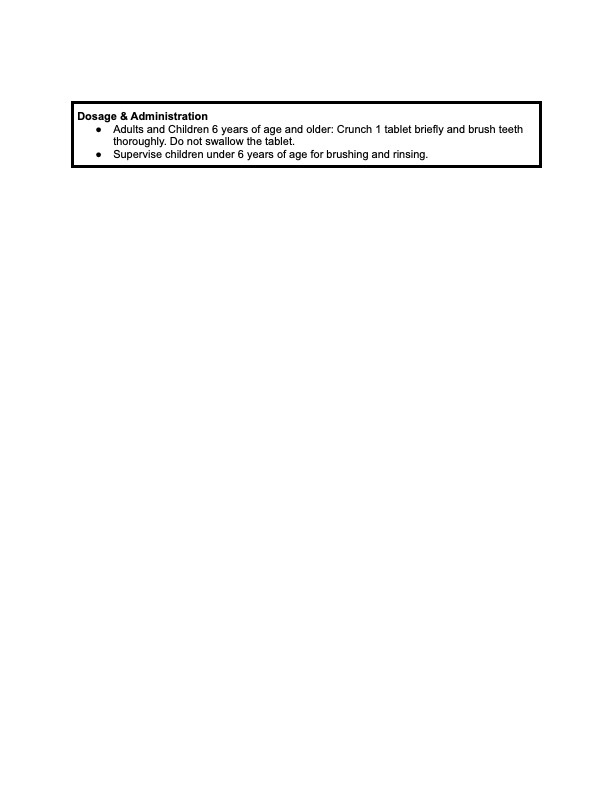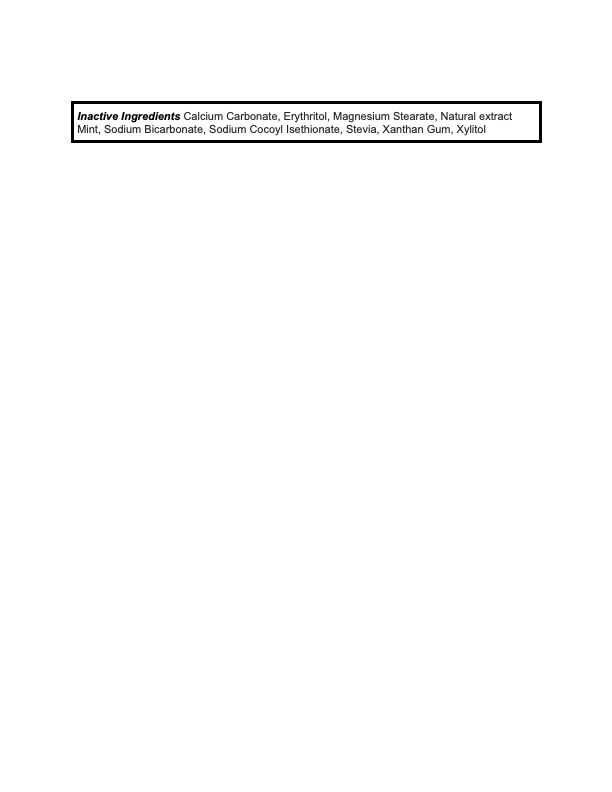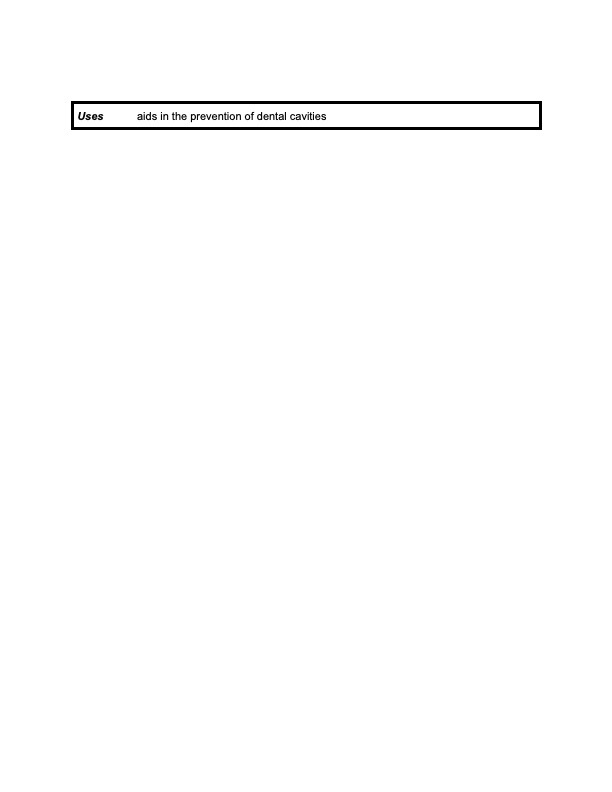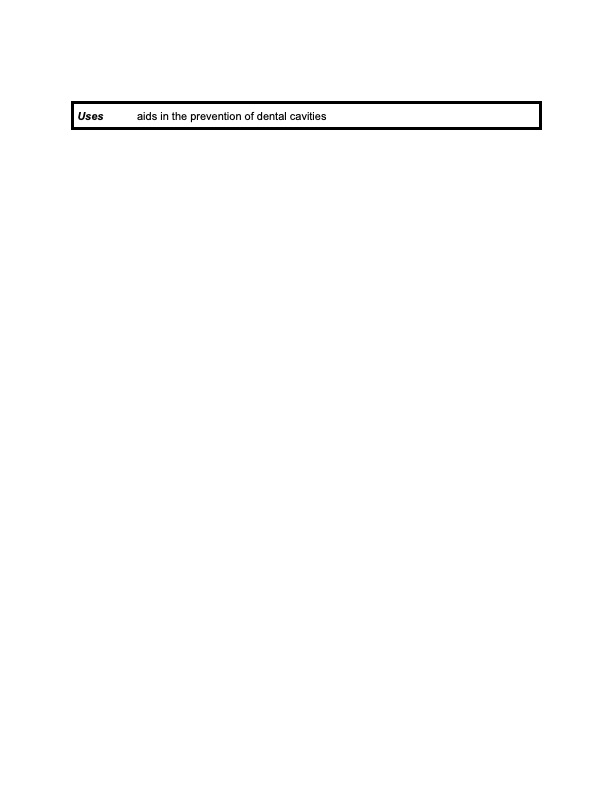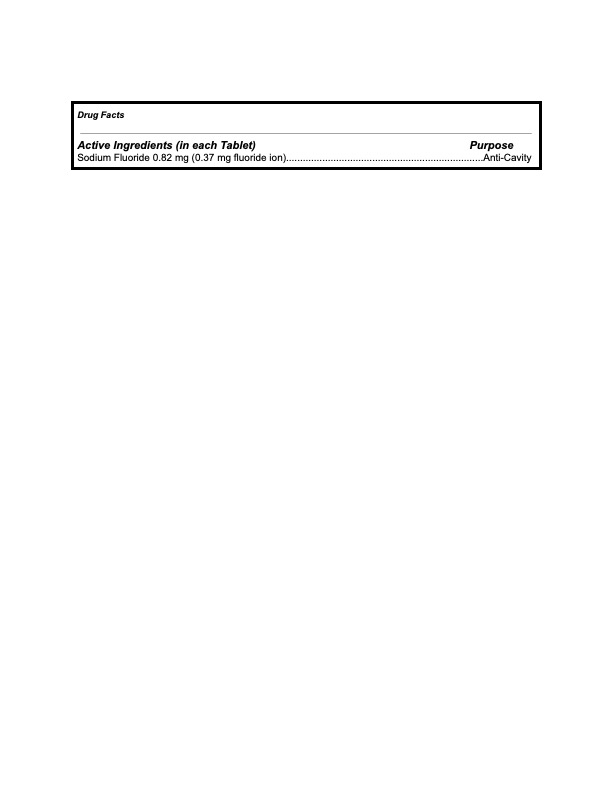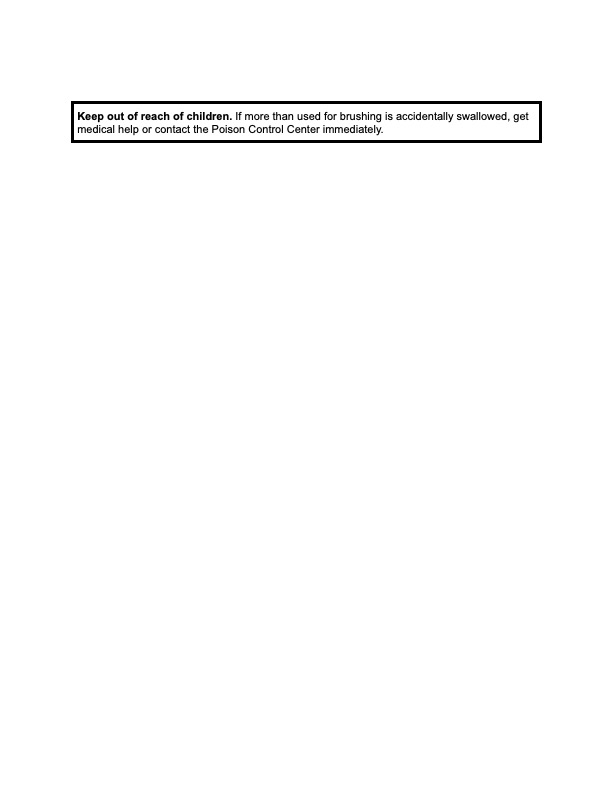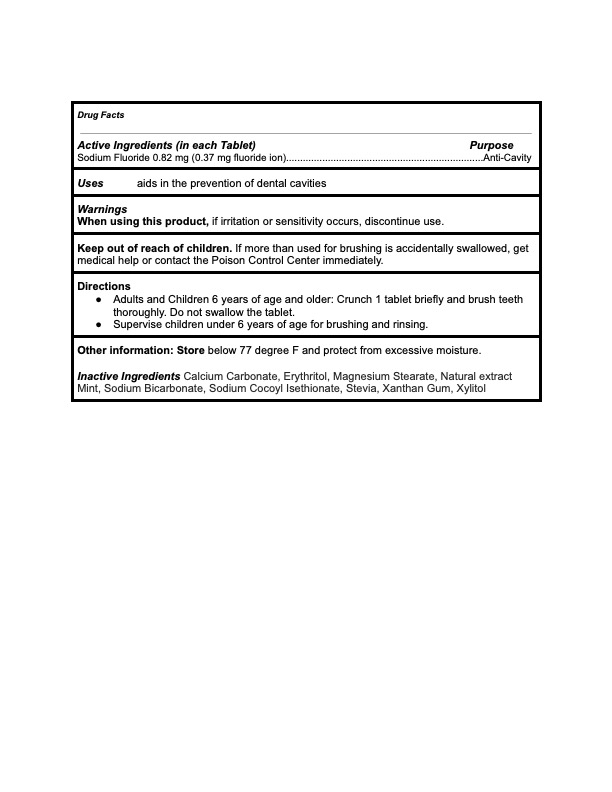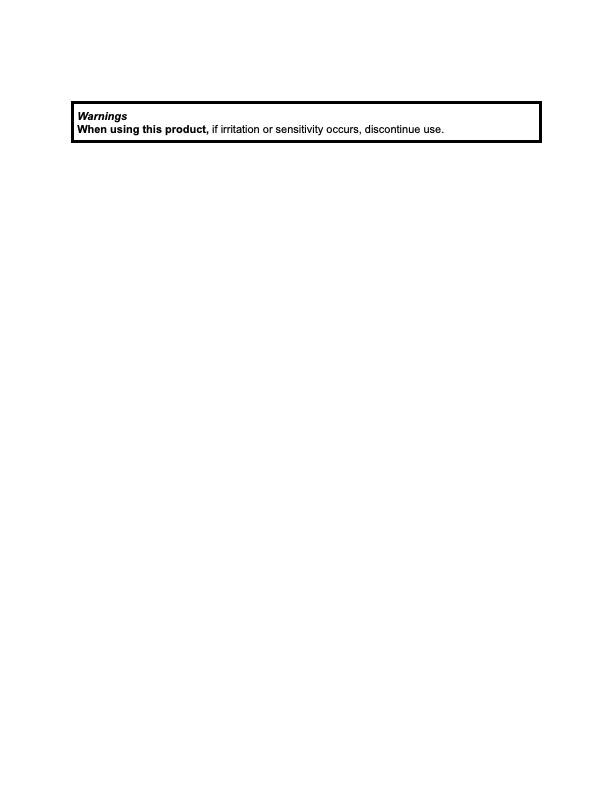 DRUG LABEL: KAYLAAN
NDC: 82091-112 | Form: TABLET, CHEWABLE
Manufacturer: Kaylaan LLC
Category: otc | Type: HUMAN OTC DRUG LABEL
Date: 20250116

ACTIVE INGREDIENTS: SODIUM FLUORIDE 0.37 mg/440 mg
INACTIVE INGREDIENTS: CALCIUM CARBONATE; STEVIA LEAF; ERYTHRITOL; MAGNESIUM STEARATE; SODIUM BICARBONATE; SODIUM COCOYL ISETHIONATE; XANTHAN GUM; MINT; XYLITOL

Kaylaan Mint Toothpaste Tablet Refill

RECENT MAJOR CHANGES

Dosage and Adminstration section falls under direction.

INDICATION AND USAGE updated